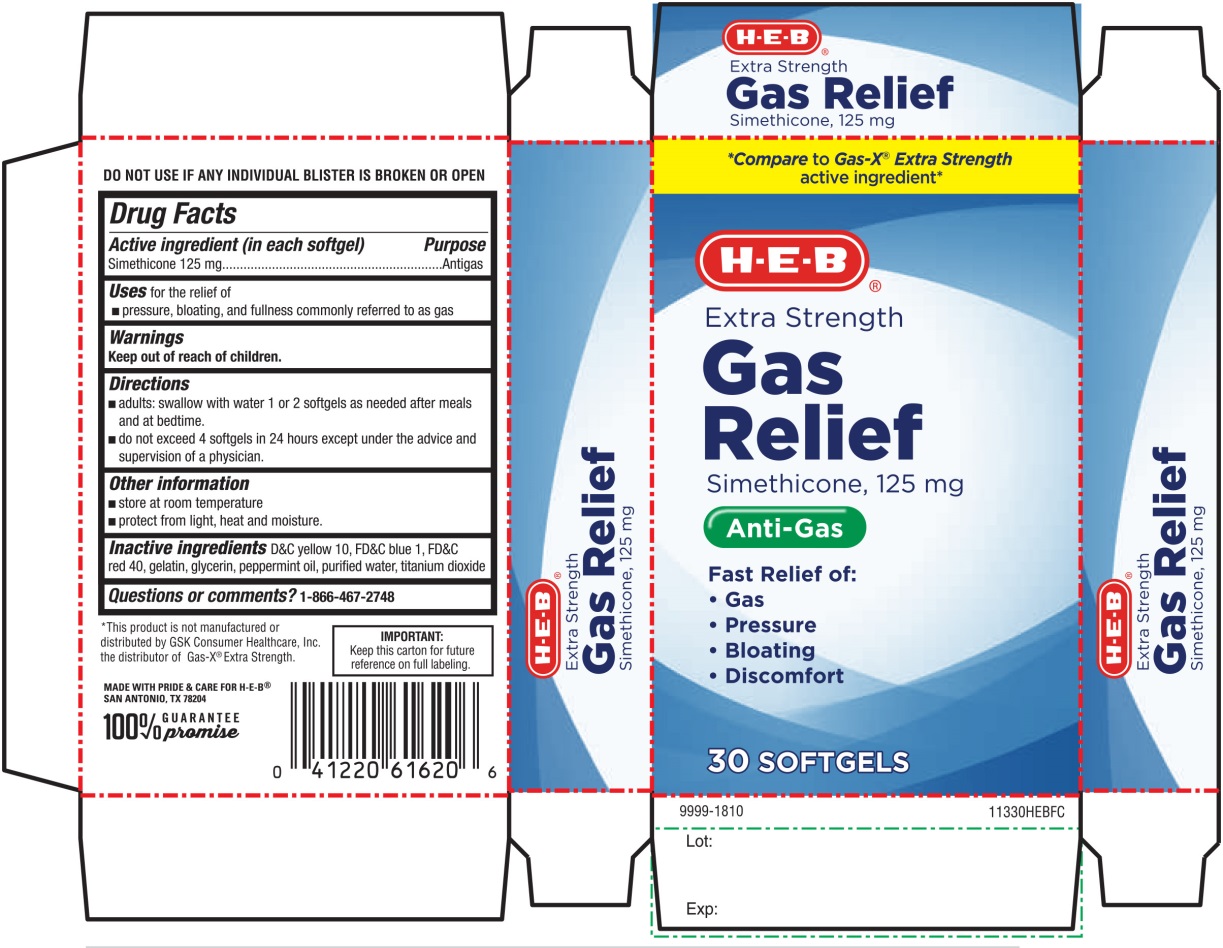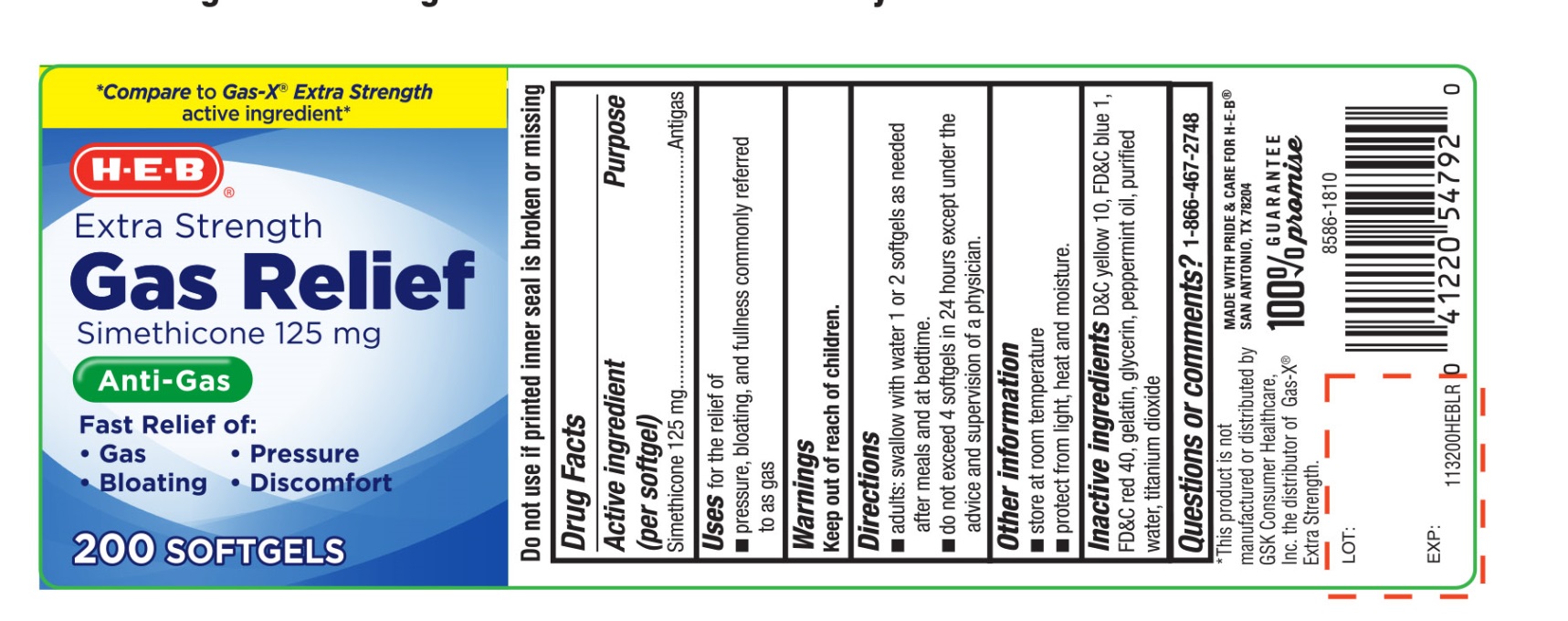 DRUG LABEL: HEB Anti Gas

NDC: 37808-231 | Form: CAPSULE, LIQUID FILLED
Manufacturer: HEB
Category: otc | Type: HUMAN OTC DRUG LABEL
Date: 20251003

ACTIVE INGREDIENTS: DIMETHICONE, UNSPECIFIED 125 mg/1 1
INACTIVE INGREDIENTS: D&C YELLOW NO. 10; FD&C BLUE NO. 1; FD&C RED NO. 40; GELATIN, UNSPECIFIED; GLYCERIN; PEPPERMINT OIL; WATER; TITANIUM DIOXIDE

HEB Extra Strength Gas Relief Softgels Drug Facts

Active ingredient (in each softgel)

Simethicone 125 mg

Purpose

Antigas

Uses

for the relief of:

- pressure
- bloating and
- fullness commonly referred to as gas

Directions

- adults:swallow with water 1 or 2 softgels as needed after meals and at bedtime.
- do not exceed 4 softgels in 24 hours except under the advice and supervision of a physician.

Other information

- store at room temperature
- protect from light, heat and moisture.

Inactive ingredients

D&C yellow #10, FD&C blue #1, FD&C red #40, gelatin, glycerin, peppermint oil, purified water, titanium dioxide.

Questions or comments?

1-866-467-2748

Principal Display Panel

H-E-B®

*Compare to Gas-X®Extra Strength active ingredient*

Extra Strength

Gas Relief

Simethicone 125 mg

Anti-Gas

Fast Relief of:

- Gas
- Pressure
- Bloating
- Discomfort

100% GURANTEE promise

IMPORTANT: Keep this carton for future reference on full labeling.

MADE WITH PRIDE & CARE FOR H-E-B®SAN ANTONIO, TX 78204

DO NOT USE IF ANY INDIVIDUAL BLISTER UNIT IS BROKEN OR OPEN.

*This product is not manufactured or distributed by GSK Consumer Healthcare, Inc. the distributor of Gas-X®Extra Strength.

Package Label 200 Softgels